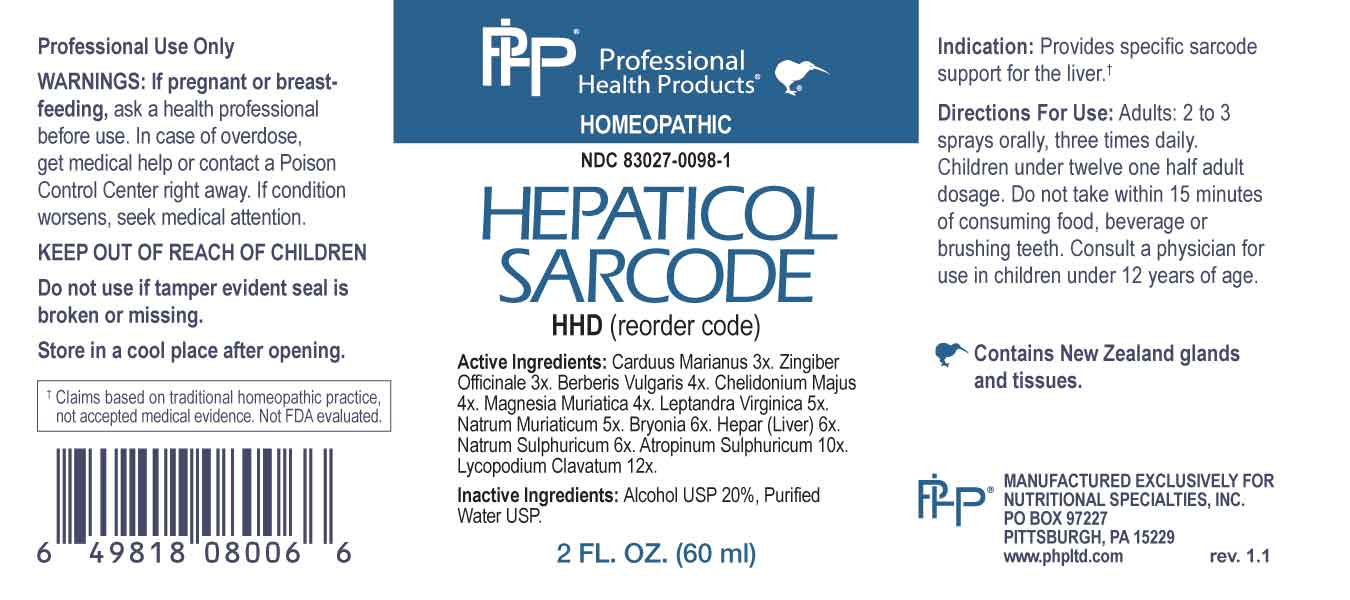 DRUG LABEL: Hepaticol Sarcode
NDC: 83027-0098 | Form: SPRAY
Manufacturer: Nutritional Specialties, Inc.
Category: homeopathic | Type: HUMAN OTC DRUG LABEL
Date: 20230814

ACTIVE INGREDIENTS: MILK THISTLE 3 [hp_X]/1 mL; GINGER 3 [hp_X]/1 mL; BERBERIS VULGARIS ROOT BARK 4 [hp_X]/1 mL; CHELIDONIUM MAJUS WHOLE 4 [hp_X]/1 mL; MAGNESIUM CHLORIDE 4 [hp_X]/1 mL; VERONICASTRUM VIRGINICUM ROOT 5 [hp_X]/1 mL; SODIUM CHLORIDE 5 [hp_X]/1 mL; BRYONIA ALBA ROOT 6 [hp_X]/1 mL; BEEF LIVER 6 [hp_X]/1 mL; SODIUM SULFATE 6 [hp_X]/1 mL; ATROPINE SULFATE 10 [hp_X]/1 mL; LYCOPODIUM CLAVATUM SPORE 12 [hp_X]/1 mL
INACTIVE INGREDIENTS: WATER; ALCOHOL

DRUG FACTS:

ACTIVE INGREDIENTS:

Carduus Marianus3X, Zingiber Officinale 3X, Berberis Vulgaris 4X, Chelidonium Majus 4X, Magnesia Muriatica 4X, Leptandra Virginica 5X, Natrum Muriaticum 5X, Bryonia 6X, Hepar (Liver) 6X, Natrum Sulphuricum 6X, Atropinum Sulphuricum 10X, Lycopodium Clavatum 12X.

PURPOSE:

Provides specific sarcode support for the liver.†

†Claims based on traditional homeopathic practice, not accepted medical evidence. Not FDA evaluated.

WARNINGS:

Professional Use Only

If pregnant or breast-feeding, ask a health professional before use.

In case of overdose, get medical help or contact a Poison Control Center right away.

If condition worsens, seek medical attention.

KEEP OUT OF REACH OF CHILDREN

Do not use if tamper evident seal is broken or missing.

Store in a cool place after opening

KEEP OUT OF REACH OF CHILDREN:

In case of overdose, get medical help or contact a Poison Control Center right away.

DIRECTIONS:

Adults: 2 to 3 sprays orally, three times daily. Children under twelve one half adult dosage. Do not take within 15 minutes of consuming food, beverage or brushing teeth. Consult a physician for use in children under 12 years of age.

INDICATIONS:

Provides specific sarcode support for the liver.†

†Claims based on traditional homeopathic practice, not accepted medical evidence. Not FDA evaluated.

INACTIVE INGREDIENTS:

Alcohol USP 20%, Purified Water USP.

QUESTIONS:

MANUFACTURED EXCLUSIVELY FOR

NUTRITIONAL SPECIALTIES, INC.

PO BOX 97227

PITTSBURG, PA 15229

www.phpltd.com

PACKAGE LABEL DISPLAY:

Professional

Health Products

HOMEOPATHIC

NDC 83027-0098-1

HEPATICOL

SARCODE

2 FL. OZ (60 ml)